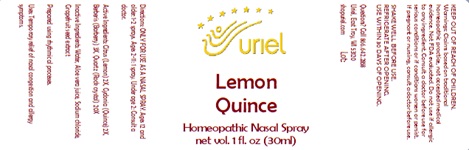 DRUG LABEL: Lemon Quince
NDC: 48951-6086 | Form: SPRAY
Manufacturer: Uriel Pharmacy Inc.
Category: homeopathic | Type: HUMAN OTC DRUG LABEL
Date: 20241212

ACTIVE INGREDIENTS: LEMON JUICE 2 [hp_X]/1 mL; QUINCE 2 [hp_X]/1 mL; BERBERIS VULGARIS ROOT BARK 3 [hp_X]/1 mL; SILICON DIOXIDE 20 [hp_X]/1 mL
INACTIVE INGREDIENTS: WATER; ALOE VERA LEAF; SODIUM CHLORIDE; CITRUS PARADISI SEED

Lemon Quince

INDICATIONS AND USAGE

Directions: ONLY FOR USE AS A NASAL SPRAY.

DOSAGE AND ADMINISTRATION

Ages 12 and older: 2-3 sprays. Ages 2-11: 1-2 sprays. Under age 2: Consult a doctor.

ACTIVE INGREDIENT

Active Ingredients: Citrus (Lemon) 2X, Cydonia (Quince) 2X, Berberis (Barberry) 3X, Quartz (Rock crystal) 20X

INACTIVE INGREDIENT

Inactive Ingredients: Distilled water, Aloe vera juice, Sodium chloride, Grapefruit seed extract

Prepared using rhythmical processes.

PURPOSE

Use: Temporary relief of nasal congestion and allergy symptoms.

KEEP OUT OF REACH OF CHILDREN.

WARNINGS

Warnings: Claims based on traditional homeopathic practice, not accepted medical evidence. Not FDA evaluated. Do not use if allergic to any ingredient. Consult a doctor before use for serious conditions or if conditions worsen or persist. If pregnant or nursing, consult a doctor before use. Do not use if safety seals on box are broken or missing.

SHAKE WELL BEFORE USE.
REFRIGERATE AFTER OPENING.
USE WITHIN 30 DAYS OF OPENING.

QUESTIONS

Questions? Call 866.642.2858 Uriel, East Troy, WI 53120 shopuriel.com Lot: